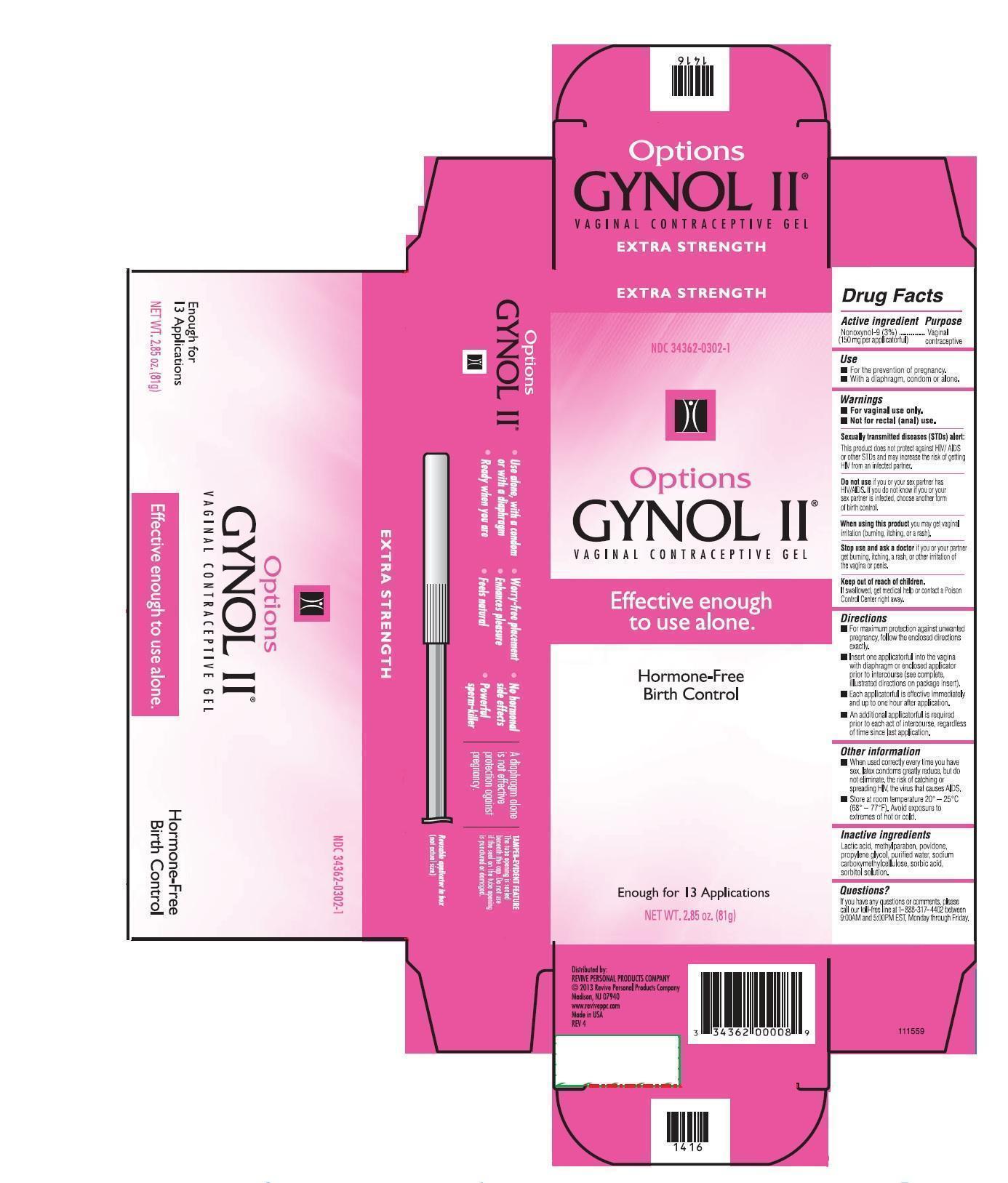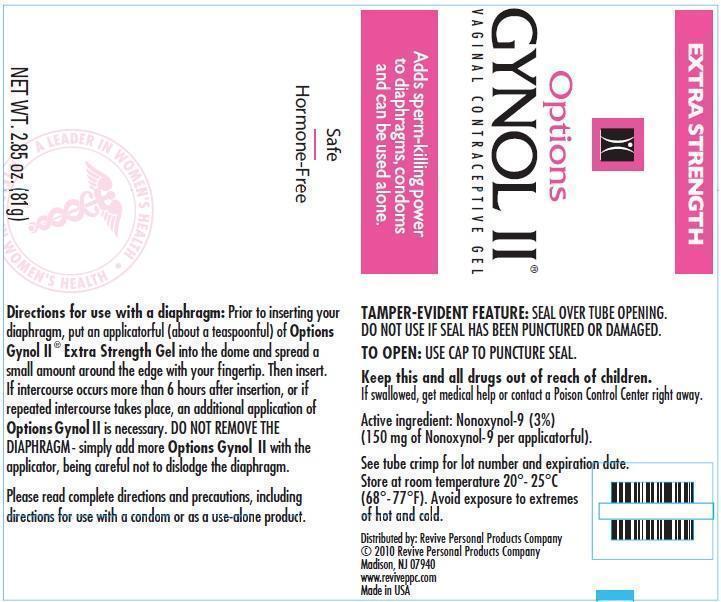 DRUG LABEL: Gynol II
NDC: 34362-0302 | Form: GEL
Manufacturer: Caldwell Consumer Health LLC
Category: otc | Type: HUMAN OTC DRUG LABEL
Date: 20201201

ACTIVE INGREDIENTS: NONOXYNOL-9 3.0 g/100 g
INACTIVE INGREDIENTS: WATER; SORBITOL; SORBIC ACID; METHYLPARABEN; LACTIC ACID; POVIDONE K29/32; PROPYLENE GLYCOL; CARBOXYMETHYLCELLULOSE SODIUM

Drug Facts

Active ingredient

Nonoxynol-9 (3%) (100 mg per applicatorful)............................................Vaginal Contraceptive

Uses

For the prevention of pregnancy.

With condom or alone.

WARNINGS

For vaginal use only.

Not for rectal (anal) use.

Sexually transmitted diseases (STDs) alert:

This product does not protect against HIV/AIDS or other STDs and may increase the risk of getting HIV from an infected partner.

Do not use if you or your sex partner has HIV/AIDS. If you do not know if your sex partner is infected, choose another form of birth control.

Stop use and ask a doctor if you or your partner gets burning, itching, a rash, or other irritation or the vagina or penis.

Keep out of reach of children if swallowed, get medical help or contact a Poison Control Center right away.

Directions

For maximum protection against unwanted pregnancy, follow the enclosed directions exactly.

Each applicatorful is effective immediately and up to one hour after application.

DOSAGE AND ADMINISTRATION

Insert one applicatorful into the vagina prior to intercourse (see complete, illustrated directions on the package insert).

An additional applicatorful is required prior to each act of intercourse, regardless of time since last application.

Other Information

When used correctly every time you have sex, latex condoms greatly reduce, but do not eliminate, the risk of catching or spreading HIV, the virus that causes AIDS.

Store at room temperature, 20° - 25° C (68° -77° F). Avoid exposure to extremes of hot or cold.

Inactive ingredients

Lactic acid, methylparaben, povidone, propylene glycol, purified water, sodium carboxymethylcellulose, sorbic acid, sorbitol solution.

PACKAGE LABEL

mm1.jpg

MM2.jpg